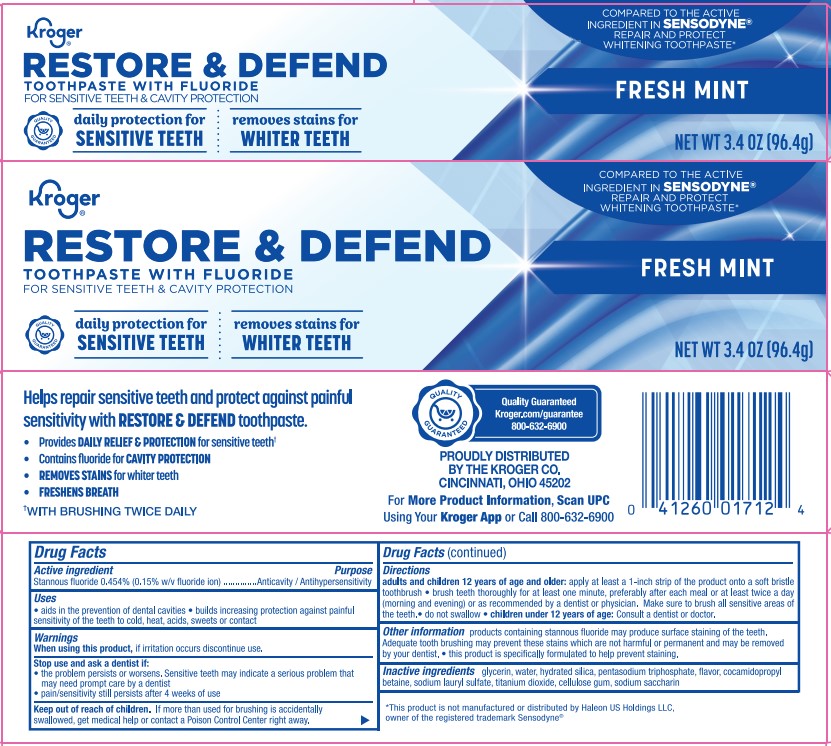 DRUG LABEL: Restore and Defend Whitening TP
NDC: 30142-256 | Form: PASTE, DENTIFRICE
Manufacturer: Kroger
Category: otc | Type: HUMAN OTC DRUG LABEL
Date: 20251113

ACTIVE INGREDIENTS: STANNOUS FLUORIDE 0.15 g/100 g
INACTIVE INGREDIENTS: SODIUM TRIPOLYPHOSPHATE ANHYDROUS; CARBOXYMETHYLCELLULOSE SODIUM; COCAMIDOPROPYL BETAINE; HYDRATED SILICA; SODIUM LAURYL SULFATE; GLYCERIN; WATER; SACCHARIN SODIUM; TITANIUM DIOXIDE

5820083 Kroger Restore & Defend Whitening (80-15274)

ACTIVE INGREDIENT

Stannous fluoride 0.454% (0.15% w/v fluoride ion)

INACTIVE INGREDIENT

glycerin, water, hydrated silica, pentasodium triphosphate, cellulose gum, cocamidopropyl betaine, flavor, sodium lauryl sulfate, titanium dioxide, sodium saccharin

PURPOSE

Anticavity, Antihypersensitivity

INDICATIONS AND USAGE

aids in the prevention of dental cavities

builds increasing protection against painful sensitivity of the teeth to cold, heat, acids, sweets or contact

When using this product, if irritation occurs discontinue use.

Stop using and ask a dentist if:

- the problem persists or worsens. Sensitive teeth may indicate a serious problem that may need prompt care by a dentist

- pain/sensitivty still persists after 4 weeks of use

Keep out of reach of children.

Keep out of reach of children. If more than used for brushing is accidentally swallowed, get medical help or contact a Poison Control Center right away.

DOSAGE AND ADMINISTRATION

Directions adults and children 12 years of age and older: apply at least a 1-inch strip of the product onto a soft bristle toothbrush • brush teeth thoroughly for at least one minute, preferably after each emal or at least twice a day (morning and evening) or as recommended by a dentist or physician.

Make sure to brush all sensitive areas of the teeth. Do not swallow. • children under 12 years of age: Consult a dentist or doctor.